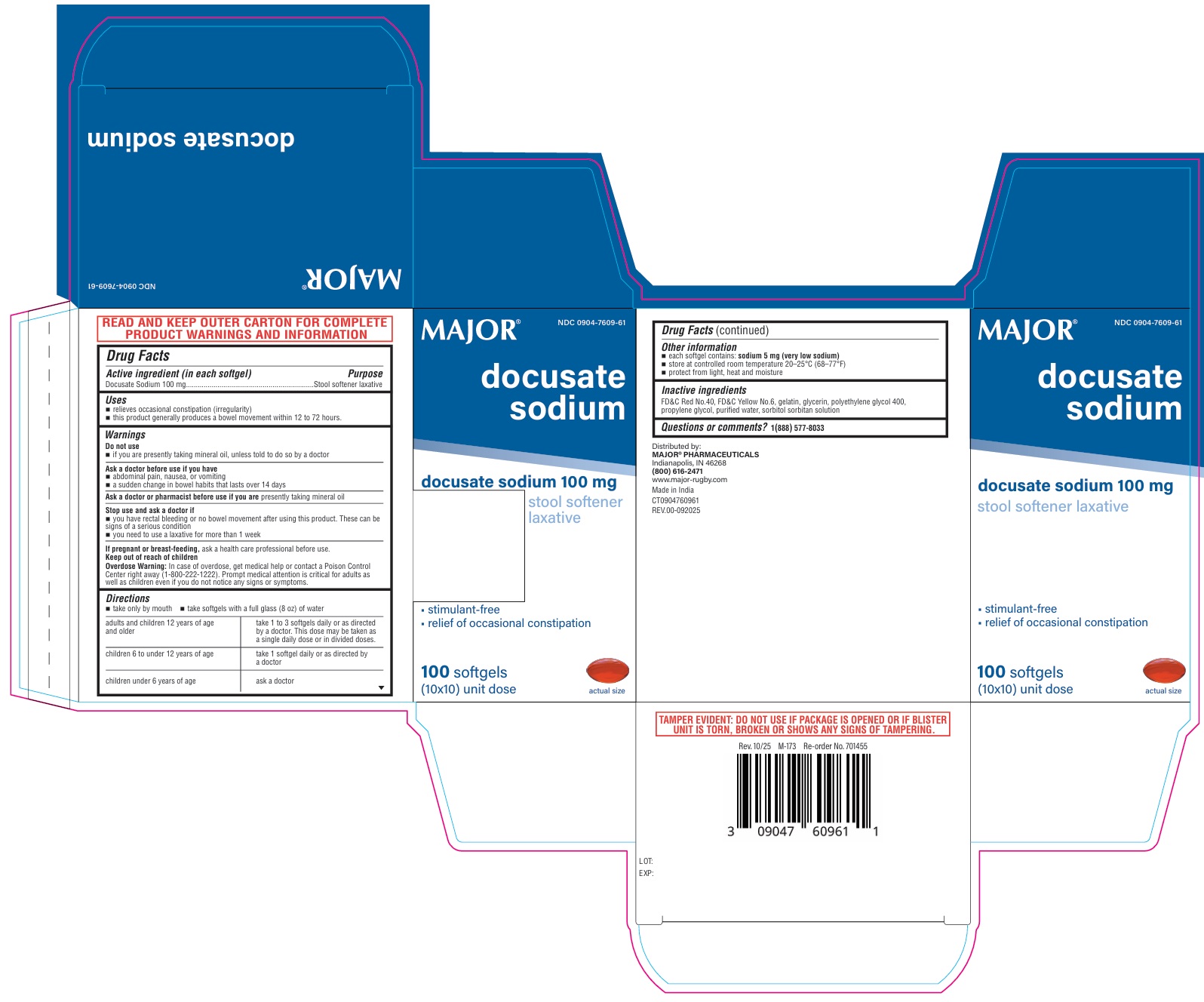 DRUG LABEL: Docusate Sodium
NDC: 0904-7609 | Form: CAPSULE, LIQUID FILLED
Manufacturer: Major Pharmaceuticals
Category: otc | Type: HUMAN OTC DRUG LABEL
Date: 20251210

ACTIVE INGREDIENTS: DOCUSATE SODIUM 100 mg/1 1
INACTIVE INGREDIENTS: FD&C RED NO. 40; FD&C YELLOW NO. 6; GELATIN, UNSPECIFIED; GLYCERIN; POLYETHYLENE GLYCOL 400; PROPYLENE GLYCOL; WATER; SORBITOL; SORBITAN

MAJOR® docusate sodium stool softener laxative

Active ingredient (in each softgel)

Docusate Sodium 100 mg

Purpose

Stool softener laxative

Uses

• relieves occasional constipation (irregularity)
• this product generally produces a bowel movement within 12 to 72 hours.

Warnings

Do not use
• if you are presently taking mineral oil, unless told to do so by a doctor

Ask a doctor before use if you have
• abdominal pain, nausea, or vomiting
• a sudden change in bowel habits that lasts over 14 days

Ask a doctor or pharmacist before use if you are presently taking mineral oil

Stop use and ask a doctor if
• you have rectal bleeding or no bowel movement after using this product. These can be signs of a serious condition
• you need to use a laxative for more than 1 week

If pregnant or breast-feeding, ask a health care professional before use.

Keep out of reach of children
Overdose Warning: In case of overdose, get medical help or contact a Poison Control Center right away (1-800-222-1222). Prompt medical attention is critical for adults as well as children even if you do not notice any signs or symptoms.

Directions

• take only by mouth • take softgels with a full glass (8 oz) of water

adults and children 12 years of age and older | take 1 to 3 softgels daily or as directed by a doctor. This dose may be taken as a single daily dose or in divided doses.
children 6 to under 12 years of age | take 1 softgel daily or as directed by a doctor
children under 6 years of age | ask a doctor

Other information

• each softgel contains: sodium 5 mg (very low sodium)
• store at controlled room temperature 20–25°C (68–77°F)
• protect from light, heat and moisture

Inactive ingredients

FD&C Red No.40, FD&C Yellow No.6, gelatin, glycerin, polyethylene glycol 400, propylene glycol, purified water, sorbitol sorbitan solution

Questions or comments?

1(888) 577-8033

NDC 0904-7609-61

MAJOR® docusate sodium

docusate sodium 100 mg

stool softener
laxative

• stimulant-free
• relief of occasional constipation

100 softgels

(10x10) unit dose

Distributed by:
MAJOR® PHARMACEUTICALS
Indianapolis, IN 46268
(800) 616-2471

www.major-rugby.com
Made in India
CT0904760961
REV.00-092025

Rev. 10/25 M-173 Re-order No. 701455

READ AND KEEP OUTER CARTON FOR COMPLETE
PRODUCT WARNINGS AND INFORMATION

TAMPER EVIDENT: DO NOT USE IF PACKAGE IS OPENED OR IF BLISTER
UNIT IS TORN, BROKEN OR SHOWS ANY SIGNS OF TAMPERING.